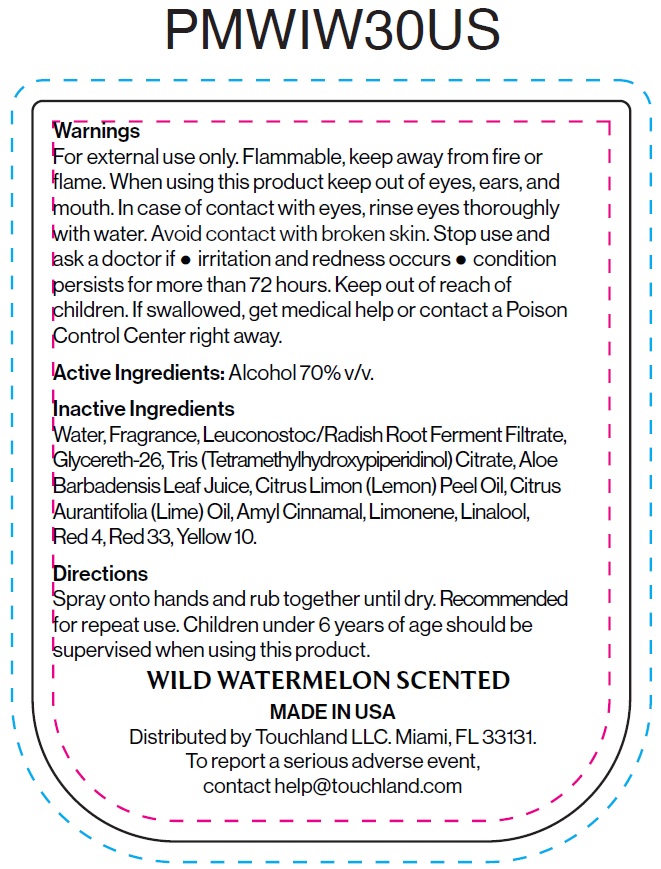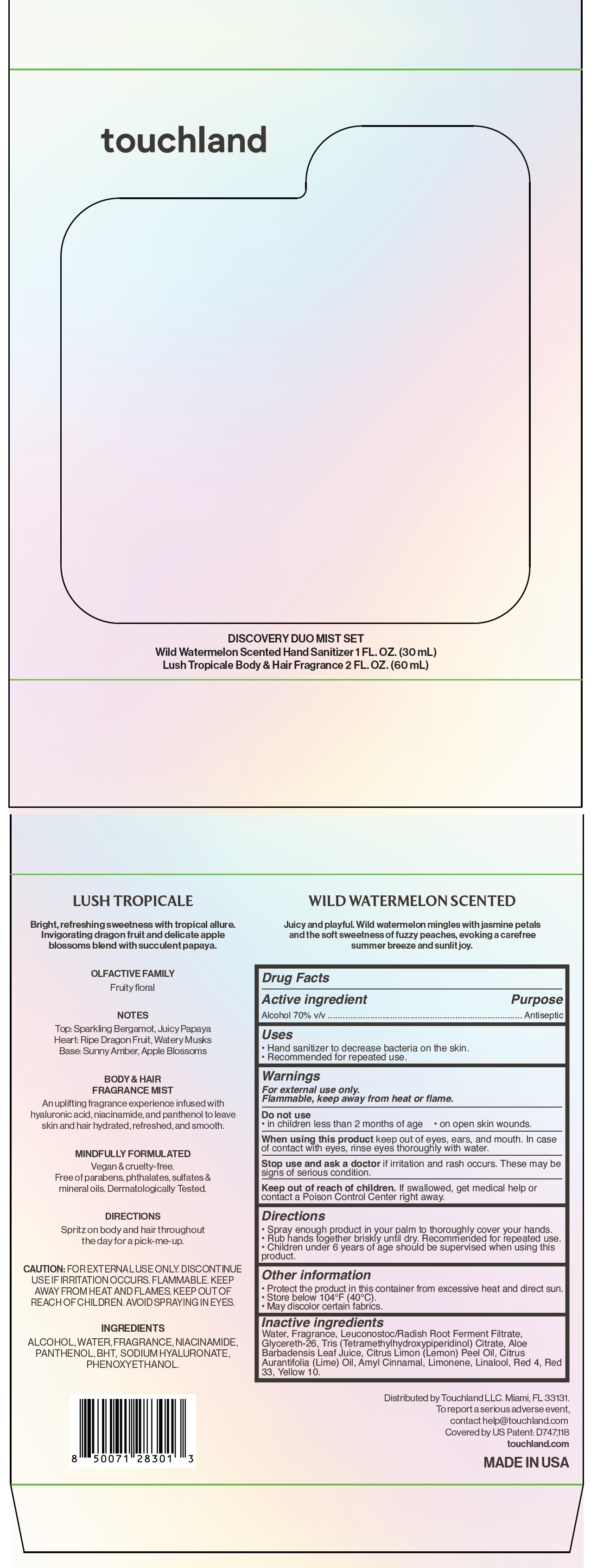 DRUG LABEL: Touchland Discovery Duo Mist Set Wild Watermelon Scented Hand Sanitizer and Lush Tropicale Body and Hair Fragrance
NDC: 72033-152 | Form: KIT | Route: TOPICAL
Manufacturer: TOUCHLAND LLC
Category: otc | Type: HUMAN OTC DRUG LABEL
Date: 20250702

ACTIVE INGREDIENTS: ALCOHOL 70 mL/100 mL
INACTIVE INGREDIENTS: WATER; LEUCONOSTOC/RADISH ROOT FERMENT FILTRATE; GLYCERETH-26; TRIS(TETRAMETHYLHYDROXYPIPERIDINOL) CITRATE; ALOE VERA LEAF JUICE; LEMON OIL, COLD PRESSED; LIME OIL, COLD PRESSED; .ALPHA.-AMYLCINNAMALDEHYDE; LIMONENE, (+)-; LINALOOL, (+/-)-; FD&C RED NO. 4; D&C RED NO. 33; D&C YELLOW NO. 10

Touchland Discovery Duo Mist Set, Wild Watermelon Scented Hand Sanitizer and Lush Tropicale Body & Hair Fragrance

Active ingredient

Alcohol 70% v/v

Purpose

Antiseptic

Uses

- Hand sanitizer to decrease bacteria on the skin.
- Recommended for repeated use.

Warnings

For external use only.

Flammable, keep away from heat or flame.

Do not use

- in children less than 2 months of age
- on open skin wounds

When using this product

keep out of eyes, ears and mouth. In case of contact with eyes, rinse eyes thoroughly with water.

Stop use and ask a doctor

if irritation and rash occurs. These may be sings of serious condition.

Keep out of reach of children.

If swallowed, get medical help or contact a Poison Control Center right away.

Directions

- Spray enough product in your palm to thoroughly cover your hands.
- Rub hands together briskly until dry. Recommended for repeated use.
- Children under 6 years of age should be supervised when using this product.

Other information

- Protect the product in this container from excessive heat and direct sun.
- Store below 104°F (40°C).
- May discolor certain fabrics.

Inactive ingredients

Water, Fragrance, Leuconostoc/Radish Root Ferment Filtrate, Glycereth-26, Tris (Tetramethylhydroxypiperidinol) Citrate, Aloe Barbadensis Leaf Juice, Citrus Limon (Lemon) Peel Oil, Citrus Aurantifolia (Lime) Oil, Amyl Cinnamal, Limonene, Linalool, Red 4, Red 33, Yellow 10.